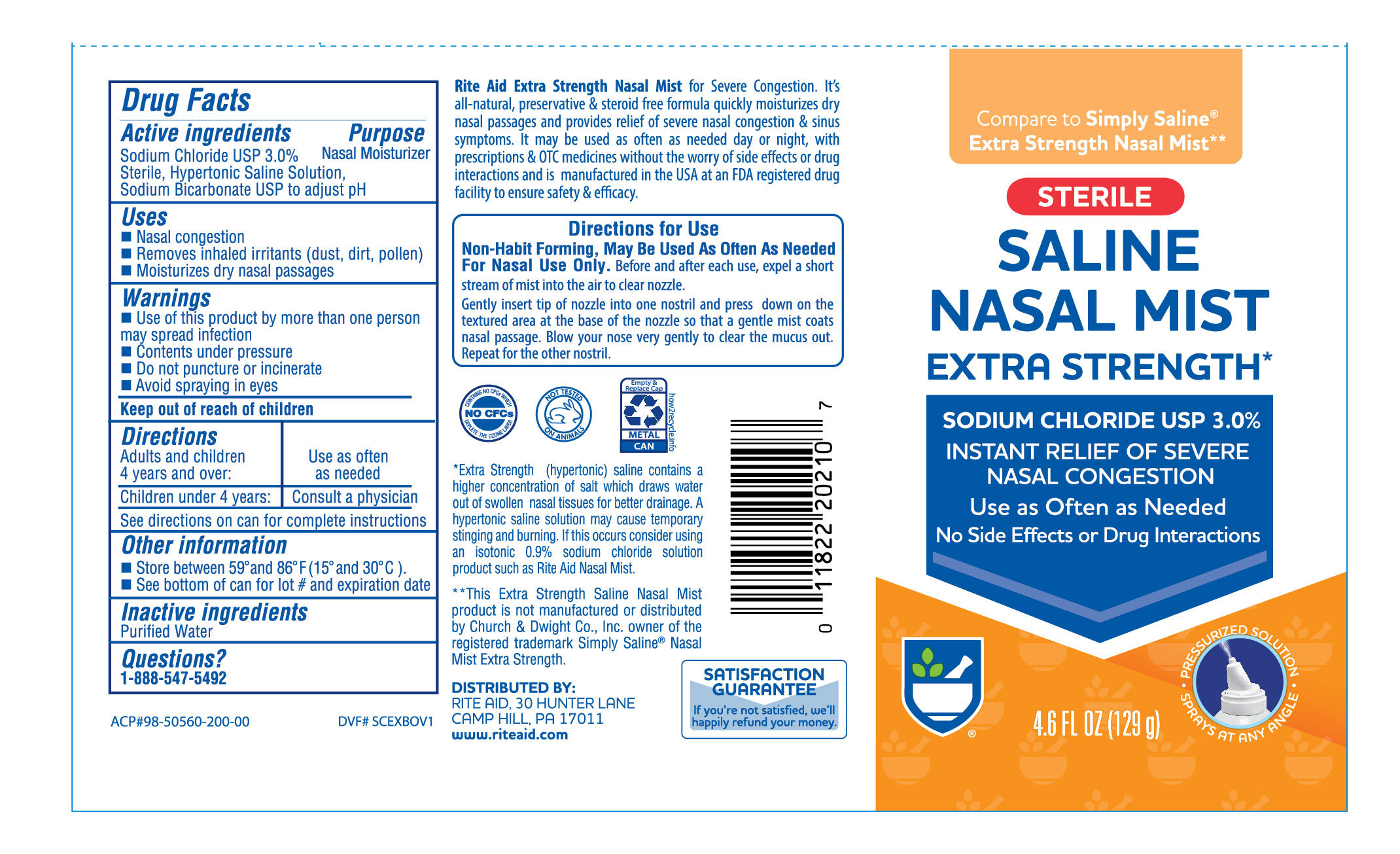 DRUG LABEL: Extra Strenght Saline Mist
NDC: 11822-0470 | Form: SPRAY
Manufacturer: RITE AID CORPORATION
Category: otc | Type: HUMAN OTC DRUG LABEL
Date: 20220116

ACTIVE INGREDIENTS: SODIUM CHLORIDE 3 g/100 g
INACTIVE INGREDIENTS: SODIUM BICARBONATE; WATER

Rite Aid Extra Strength Nasal Saline Mist

Active Ingredient

Sodium Chloride 3.0%

Sterile, Hypertonic Saline Solution,

Sodium Bicarbonate to adjust pH

Purpose

Nasal Wash

Uses

- Nasal congestion
- Removes inhaled irritants (dust, dirt, pollen)
- Moisturizes dry nasal passages

Directions

Adults and children 4 years and over: Use as often as needed
Children under 4 years: Consult a physician
See directions on can for complere instructions

Warnings

- Use of this product by more than one person may spread infection
- Contents under pressure
- Do not puncture or incinerate
- Avoid spraying in eyes

Keep out of reach of chlidren.

Adults and children 4 years and over: | Use as often as needed
Children under 4 years: | Consult a physician

See directions on can for complere instructions

Inactive ingredients

Purfied Water